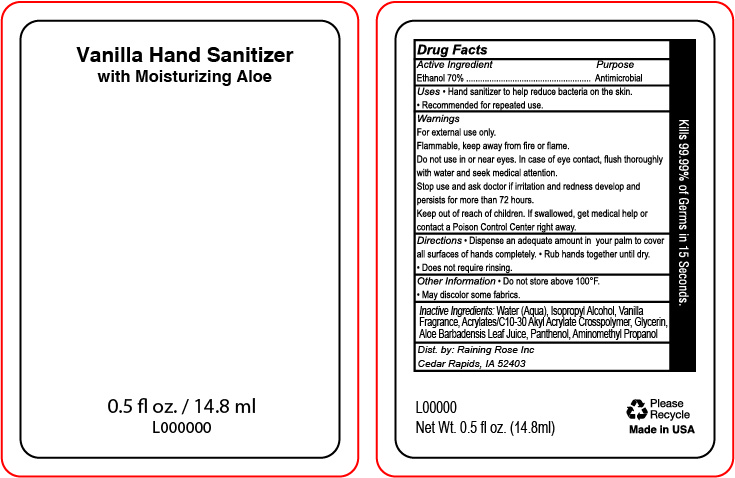 DRUG LABEL: Hand Sanitizer
NDC: 65692-2071 | Form: GEL
Manufacturer: Raining Rose
Category: otc | Type: HUMAN OTC DRUG LABEL
Date: 20210506

ACTIVE INGREDIENTS: ALCOHOL 70 mL/100 mL
INACTIVE INGREDIENTS: GLYCERIN; AMINOMETHYL PROPANEDIOL; ISOPROPYL ALCOHOL; ALOE VERA LEAF; PANTHENOL; WATER; CARBOMER INTERPOLYMER TYPE A (ALLYL SUCROSE CROSSLINKED)

ACTIVE INGREDIENT

Ethanol 70%

PURPOSE

Antimicrobial

INDICATIONS AND USAGE

Hand sanitizer to help reduce bacteria on the skin. Recommended for repeated use.

WARNINGS

For external use only. Flammable, keep away from fire or flame. Do not use in or near eyes. In case of eye contact, flush thoroughly with water and seek medical attention. Stop use and ask doctor if irritation and redness develop and persists for more than 72 hours. If swallowed, get medical help or contact a Poison Control Center right away.

Keep out of reach of children

DOSAGE AND ADMINISTRATION

Dispense an adequate amount in your palm to cover all surfaces of hands completely. Rub hands together until dry. Does not require rinsing.

OTHER SAFETY INFORMATION

Do not store above 100 degrees F. May discolor some fabrics.

INACTIVE INGREDIENT

Water (Aqua), Isopropyl Alcohol, Vanilla Fragrance, Acrylates/C10-30 Akyl Acrylate Crosspolymer, Glycerin, Aloe Barbadensis Leaf Juice, Panthenol, Aminomethyl Propanol.